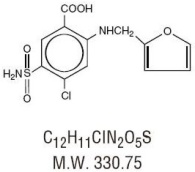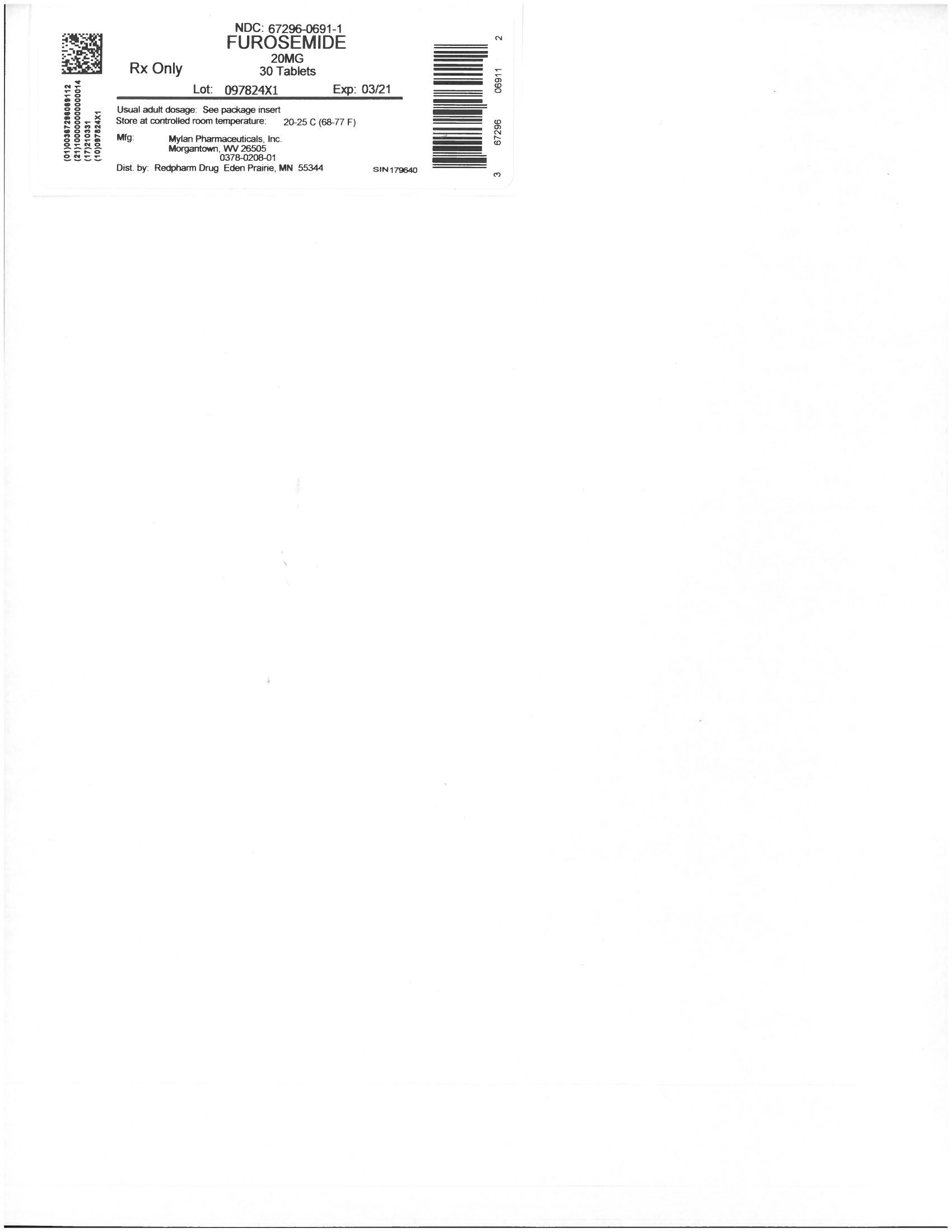 DRUG LABEL: Furosemide
NDC: 67296-0691 | Form: TABLET
Manufacturer: RedPharm Drug, Inc.
Category: prescription | Type: HUMAN PRESCRIPTION DRUG LABEL
Date: 20210113

ACTIVE INGREDIENTS: FUROSEMIDE 20 mg/1 1
INACTIVE INGREDIENTS: SILICON DIOXIDE; LACTOSE MONOHYDRATE; MICROCRYSTALLINE CELLULOSE; STARCH, CORN; STEARIC ACID

furosemide 20mg

WARNING

Furosemide is a potent diuretic which, if given in excessive amounts, can lead to a profound diuresis with water and electrolyte depletion. Therefore, careful medical supervision is required and dose and dose schedule must be adjusted to the individual patient's needs. (See DOSAGE AND ADMINISTRATION.)

DESCRIPTION

Furosemide is a diuretic which is an anthranilic acid derivative. Chemically, it is 4-Chloro- N-furfuryl-5-sulfamoylanthranilic acid. Furosemide, USP is a white to slightly yellow odorless, crystalline powder. It is practically insoluble in water, sparingly soluble in alcohol, freely soluble in dilute alkali solutions and insoluble in dilute acids.

The structural formula is as follows:

Each tablet for oral administration contains 20 mg, 40 mg or 80 mg of furosemide, USP and the following inactive ingredients: colloidal silicon dioxide, lactose monohydrate, microcrystalline cellulose, pregelatinized starch (corn) and stearic acid.

CLINICAL PHARMACOLOGY

Investigations into the mode of action of furosemide have utilized micropuncture studies in rats, stop flow experiments in dogs and various clearance studies in both humans and experimental animals. It has been demonstrated that furosemide inhibits primarily the absorption of sodium and chloride not only in the proximal and distal tubules but also in the loop of Henle. The high degree of efficacy is largely due to the unique site of action. The action on the distal tubule is independent of any inhibitory effect on carbonic anhydrase and aldosterone.

Recent evidence suggests that furosemide glucuronide is the only or at least the major biotransformation product of furosemide in man. Furosemide is extensively bound to plasma proteins, mainly to albumin. Plasma concentrations ranging from 1 to 400 mcg/mL are 91% to 99% bound in healthy individuals. The unbound fraction averages 2.3% to 4.1% at therapeutic concentrations.

The onset of diuresis following oral administration is within one hour. The peak effect occurs within the first or second hour. The duration of diuretic effect is 6 to 8 hours.

In fasted normal men, the mean bioavailability of furosemide from furosemide tablets and furosemide oral solution is 64% and 60%, respectively, of that from an intravenous injection of the drug. Although furosemide is more rapidly absorbed from the oral solution (50 minutes) than from the tablet (87 minutes), peak plasma levels and area under the plasma concentration-time curves do not differ significantly. Peak plasma concentrations increase with increasing dose but times-to-peak do not differ among doses. The terminal half-life of furosemide is approximately 2 hours.

Significantly more furosemide is excreted in urine following the IV injection than after the tablet or oral solution. There are no significant differences between the two oral formulations in the amount of unchanged drug excreted in urine.

Geriatric Population

Furosemide binding to albumin may be reduced in elderly patients. Furosemide is predominantly excreted unchanged in the urine. The renal clearance of furosemide after intravenous administration in older healthy male subjects (60 to 70 years of age) is statistically significantly smaller than in younger healthy male subjects (20 to 35 years of age). The initial diuretic effect of furosemide in older subjects is decreased relative to younger subjects. (See PRECAUTIONS: Geriatric Use.)

INDICATIONS AND USAGE

Edema

Furosemide is indicated in adults and pediatric patients for the treatment of edema associated with congestive heart failure, cirrhosis of the liver, and renal disease, including the nephrotic syndrome. Furosemide is particularly useful when an agent with greater diuretic potential is desired.

Hypertension

Oral furosemide may be used in adults for the treatment of hypertension alone or in combination with other antihypertensive agents. Hypertensive patients who cannot be adequately controlled with thiazides will probably also not be adequately controlled with furosemide alone.

CONTRAINDICATIONS

Furosemide is contraindicated in patients with anuria and in patients with a history of hypersensitivity to furosemide.

WARNINGS

In patients with hepatic cirrhosis and ascites, furosemide therapy is best initiated in the hospital. In hepatic coma and in states of electrolyte depletion, therapy should not be instituted until the basic condition is improved. Sudden alterations of fluid and electrolyte balance in patients with cirrhosis may precipitate hepatic coma; therefore, strict observation is necessary during the period of diuresis. Supplemental potassium chloride and, if required, an aldosterone antagonist are helpful in preventing hypokalemia and metabolic alkalosis.

If increasing azotemia and oliguria occur during treatment of severe progressive renal disease, furosemide should be discontinued.

Cases of tinnitus and reversible or irreversible hearing impairment and deafness have been reported. Reports usually indicate that furosemide ototoxicity is associated with rapid injection, severe renal impairment, the use of higher than recommended doses, hypoproteinemia or concomitant therapy with aminoglycoside antibiotics, ethacrynic acid, or other ototoxic drugs. If the physician elects to use high dose parenteral therapy, controlled intravenous infusion is advisable (for adults, an infusion rate not exceeding 4 mg furosemide per minute has been used). (See PRECAUTIONS: Drug Interactions).

PRECAUTIONS

General

Excessive diuresis may cause dehydration and blood volume reduction with circulatory collapse and possibly vascular thrombosis and embolism, particularly in elderly patients. As with any effective diuretic, electrolyte depletion may occur during furosemide therapy, especially in patients receiving higher doses and a restricted salt intake. Hypokalemia may develop with furosemide, especially with brisk diuresis, inadequate oral electrolyte intake, when cirrhosis is present, or during concomitant use of corticosteroids, ACTH, licorice in large amounts, or prolonged use of laxatives. Digitalis therapy may exaggerate metabolic effects of hypokalemia, especially myocardial effects.

All patients receiving furosemide therapy should be observed for these signs or symptoms of fluid or electrolyte imbalance (hyponatremia, hypochloremic alkalosis, hypokalemia, hypomagnesemia or hypocalcemia): dryness of mouth, thirst, weakness, lethargy, drowsiness, restlessness, muscle pains or cramps, muscular fatigue, hypotension, oliguria, tachycardia, arrhythmia, or gastrointestinal disturbances such as nausea and vomiting. Increases in blood glucose and alterations in glucose tolerance tests (with abnormalities of the fasting and 2-hour postprandial sugar) have been observed, and rarely, precipitation of diabetes mellitus has been reported.

In patients with severe symptoms of urinary retention (because of bladder emptying disorders, prostatic hyperplasia, urethral narrowing), the administration of furosemide can cause acute urinary retention related to increased production and retention of urine. Thus, these patients require careful monitoring, especially during the initial stages of treatment.

In patients at high risk for radiocontrast nephropathy, furosemide can lead to a higher incidence of deterioration in renal function after receiving radiocontrast compared to high-risk patients who received only intravenous hydration prior to receiving radiocontrast.

In patients with hypoproteinemia (e.g., associated with nephrotic syndrome) the effect of furosemide may be weakened and its ototoxicity potentiated.

Asymptomatic hyperuricemia can occur and gout may rarely be precipitated.

Patients allergic to sulfonamides may also be allergic to furosemide. The possibility exists of exacerbation or activation of systemic lupus erythematosus.

As with many other drugs, patients should be observed regularly for the possible occurrence of blood dyscrasias, liver or kidney damage, or other idiosyncratic reactions.

Information for Patients

Patients receiving furosemide should be advised that they may experience symptoms from excessive fluid and/or electrolyte losses. The postural hypotension that sometimes occurs can usually be managed by getting up slowly. Potassium supplements and/or dietary measures may be needed to control or avoid hypokalemia.

Patients with diabetes mellitus should be told that furosemide may increase blood glucose levels and thereby affect urine glucose tests. The skin of some patients may be more sensitive to the effects of sunlight while taking furosemide.

Hypertensive patients should avoid medications that may increase blood pressure, including over-the-counter products for appetite suppression and cold symptoms.

Laboratory Tests

Serum electrolytes (particularly potassium), CO2, creatinine and BUN should be determined frequently during the first few months of furosemide therapy and periodically thereafter. Serum and urine electrolyte determinations are particularly important when the patient is vomiting profusely or receiving parenteral fluids. Abnormalities should be corrected or the drug temporarily withdrawn. Other medications may also influence serum electrolytes.

Reversible elevations of BUN may occur and are associated with dehydration, which should be avoided, particularly in patients with renal insufficiency.

Urine and blood glucose should be checked periodically in diabetics receiving furosemide, even in those suspected of latent diabetes.

Furosemide may lower serum levels of calcium (rarely cases of tetany have been reported) and magnesium. Accordingly, serum levels of these electrolytes should be determined periodically.

In premature infants furosemide may precipitate nephrocalcinosis/nephrolithiasis, therefore renal function must be monitored and renal ultrasonography performed. (See PRECAUTIONS: Pediatric Use)

Drug Interactions

Furosemide may increase the ototoxic potential of aminoglycoside antibiotics, especially in the presence of impaired renal function. Except in life-threatening situations, avoid this combination.

Furosemide should not be used concomitantly with ethacrynic acid because of the possibility of ototoxicity. Patients receiving high doses of salicylates concomitantly with furosemide, as in rheumatic disease, may experience salicylate toxicity at lower doses because of competitive renal excretory sites.

There is a risk of ototoxic effects if cisplatin and furosemide are given concomitantly. In addition, nephrotoxicity of nephrotoxic drugs such as cisplatin may be enhanced if furosemide is not given in lower doses and with positive fluid balance when used to achieve forced diuresis during cisplatin treatment.

Furosemide has a tendency to antagonize the skeletal muscle relaxing effect of tubocurarine and may potentiate the action of succinylcholine.

Lithium generally should not be given with diuretics because they reduce lithium’s renal clearance and add a high risk of lithium toxicity.

Furosemide combined with angiotensin converting enzyme inhibitors or angiotensin II receptor blockers may lead to severe hypotension and deterioration in renal function, including renal failure. An interruption or reduction in the dosage of furosemide, angiotensin converting enzyme inhibitors, or angiotensin receptor blockers may be necessary.

Potentiation occurs with ganglionic or peripheral adrenergic blocking drugs.

Furosemide may decrease arterial responsiveness to norepinephrine. However, norepinephrine may still be used effectively.

Simultaneous administration of sucralfate and furosemide tablets may reduce the natriuretic and antihypertensive effects of furosemide. Patients receiving both drugs should be observed closely to determine if the desired diuretic and/or antihypertensive effect of furosemide is achieved. The intake of furosemide and sucralfate should be separated by at least 2 hours.

In isolated cases, intravenous administration of furosemide within 24 hours of taking chloral hydrate may lead to flushing, sweating attacks, restlessness, nausea, increase in blood pressure, and tachycardia. Use of furosemide concomitantly with chloral hydrate is therefore not recommended.

Phenytoin interferes directly with renal action of furosemide. There is evidence that treatment with phenytoin leads to decrease intestinal absorption of furosemide, and consequently to lower peak serum furosemide concentrations.

Methotrexate and other drugs that, like furosemide, undergo significant renal tubular secretion may reduce the effect of furosemide. Conversely, furosemide may decrease renal elimination of other drugs that undergo tubular secretion. High-dose treatment of both furosemide and these other drugs may result in elevated serum levels of these drugs and may potentiate their toxicity as well as the toxicity of furosemide.

Furosemide can increase the risk of cephalosporin-induced nephrotoxicity even in the setting of minor or transient renal impairment.

Concomitant use of cyclosporine and furosemide is associated with increased risk of gouty arthritis secondary to furosemide-induced hyperurecemia and cyclosporine impairment of renal urate excretion.

High doses (> 80 mg) of furosemide may inhibit the binding of thyroid hormones to carrier proteins and result in transient increase in free thyroid hormones, followed by an overall decrease in total thyroid hormone levels.

One study in six subjects demonstrated that the combination of furosemide and acetylsalicylic acid temporarily reduced creatinine clearance in patients with chronic renal insufficiency. There are case reports of patients who developed increased BUN, serum creatinine and serum potassium levels, and weight gain when furosemide was used in conjunction with NSAIDs.

Literature reports indicate that coadministration of indomethacin may reduce the natriuretic and antihypertensive effects of furosemide in some patients by inhibiting prostaglandin synthesis. Indomethacin may also affect plasma renin levels, aldosterone excretion, and renin profile evaluation. Patients receiving both indomethacin and furosemide should be observed closely to determine if the desired diuretic and/or antihypertensive effect of furosemide is achieved.

Carcinogenesis, Mutagenesis, Impairment of Fertility

Furosemide was tested for carcinogenicity by oral administration in one strain of mice and one strain of rats. A small but significantly increased incidence of mammary gland carcinomas occurred in female mice at a dose 17.5 times the maximum human dose of 600 mg. There were marginal increases in uncommon tumors in male rats at a dose of 15 mg/kg (slightly greater than the maximum human dose) but not at 30 mg/kg.

Furosemide was devoid of mutagenic activity in various strains of Salmonella typhimurium when tested in the presence or absence of an in vitro metabolic activation system, and questionably positive for gene mutation in mouse lymphoma cells in the presence of rat liver S9 at the highest dose tested. Furosemide did not induce sister chromatid exchange in human cells in vitro, but other studies on chromosomal aberrations in human cells in vitro gave conflicting results. In Chinese hamster cells it induced chromosomal damage but was questionably positive for sister chromatid exchange. Studies on the induction by furosemide of chromosomal aberrations in mice were inconclusive. The urine of rats treated with this drug did not induce gene conversion in Saccharomyces cerevisiae.

Furosemide produced no impairment of fertility in male or female rats at 100 mg/kg/day (the maximum effective diuretic dose in the rat and 8 times the maximal human dose of 600 mg/day).

Pregnancy

Furosemide has been shown to cause unexplained maternal deaths and abortions in rabbits at 2, 4 and 8 times the maximal recommended human dose. There are no adequate and well-controlled studies in pregnant women. Furosemide should be used during pregnancy only if the potential benefit justifies the potential risk to the fetus.

Treatment during pregnancy requires monitoring of fetal growth because of the potential for higher birth weights.

The effects of furosemide on embryonic and fetal development and on pregnant dams were studied in mice, rats and rabbits.

Furosemide caused unexplained maternal deaths and abortions in the rabbit at the lowest dose of 25 mg/kg (two times the maximal recommended human dose of 600 mg/day). In another study, a dose of 50 mg/kg (four times the maximal recommended human dose of 600 mg/day) also caused maternal deaths and abortions when administered to rabbits between Days 12 and 17 of gestation. In a third study, none of the pregnant rabbits survived a dose of 100 mg/kg. Data from the above studies indicate fetal lethality that can precede maternal deaths.

The results of the mouse study and one of the three rabbit studies also showed an increased incidence and severity of hydronephrosis (distention of the renal pelvis and, in some cases, of the ureters) in fetuses derived from the treated dams as compared with the incidence in fetuses from the control group.

Nursing Mothers

Because it appears in breast milk, caution should be exercised when furosemide is administered to a nursing mother.

Furosemide may inhibit lactation.

Pediatric Use

In premature infants, furosemide may precipitate nephrocalcinosis/nephrolithiasis. Nephrocalcinosis/nephrolithiasis has also been observed in children under 4 years of age with no history of prematurity who have been treated chronically with furosemide. Monitor renal function, and renal ultrasonography should be considered, in pediatric patients receiving furosemide.

If furosemide is administered to premature infants during the first weeks of life, it may increase the risk of persistence of patent ductus arteriosus.

Geriatric Use

Controlled clinical studies of furosemide did not include sufficient numbers of subjects aged 65 and over to determine whether they respond differently from younger subjects. Other reported clinical experience has not identified differences in responses between the elderly and younger patients. In general, dose selection for the elderly patient should be cautious, usually starting at the low end of the dosing range, reflecting the greater frequency of decreased hepatic, renal or cardiac function, and of concomitant disease or other drug therapy.

This drug is known to be substantially excreted by the kidney, and the risk of toxic reactions to this drug may be greater in patients with impaired renal function. Because elderly patients are more likely to have decreased renal function, care should be taken in dose selection and it may be useful to monitor renal function. (See PRECAUTIONS: General and DOSAGE AND ADMINISTRATION.)

ADVERSE REACTIONS

Adverse reactions are categorized below by organ system and listed by decreasing severity.

Gastrointestinal System Reactions

- hepatic encephalopathy in patients with hepatocellular insufficiency
- pancreatitis
- jaundice (intrahepatic cholestatic jaundice)
- increased liver enzymes
- anorexia
- oral and gastric irritation
- cramping
- diarrhea
- constipation
- nausea
- vomiting

Systemic Hypersensitivity Reactions

- severe anaphylactic or anaphylactoid reactions (e.g., with shock)
- systemic vasculitis
- interstitial nephritis
- necrotizing angiitis

Central Nervous System Reactions

- tinnitus and hearing loss
- paresthesias
- vertigo
- dizziness
- headache
- blurred vision
- xanthopsia

Hematologic Reactions

- aplastic anemia
- thrombocytopenia
- agranulocytosis
- hemolytic anemia
- leukopenia
- anemia
- eosinophilia

Dermatologic-Hypersensitivity Reactions

- toxic epidermal necrolysis
- Stevens-Johnson Syndrome
- erythema multiforme
- drug rash with eosinophilia and systemic symptoms
- acute generalized exanthematous pustulosis
- exfoliative dermatitis
- bullous pemphigoid
- purpura
- photosensitivity
- rash
- pruritus
- urticaria

Cardiovascular Reaction

- Orthostatic hypotension may occur and be aggravated by alcohol, barbiturates or narcotics.
- Increase in cholesterol and triglyceride serum levels.

Other Reactions

- hyperglycemia
- glycosuria
- hyperuricemia
- muscle spasm
- weakness
- restlessness
- urinary bladder spasm
- thrombophlebitis
- fever

Whenever adverse reactions are moderate or severe, furosemide dosage should be reduced or therapy withdrawn.

OVERDOSAGE

The principal signs and symptoms of overdosage with furosemide are dehydration, blood volume reduction, hypotension, electrolyte imbalance, hypokalemia and hypochloremic alkalosis, and are extensions of its diuretic action.

The acute toxicity of furosemide has been determined in mice, rats and dogs. In all three, the oral LD50 exceeded 1000 mg/kg body weight, while the intravenous LD50 ranged from 300 to 680 mg/kg. The acute intragastric toxicity in neonatal rats is 7 to 10 times that of adult rats.

The concentration of furosemide in biological fluids associated with toxicity or death is not known.

Treatment of overdosage is supportive and consists of replacement of excessive fluid and electrolyte losses. Serum electrolytes, carbon dioxide level and blood pressure should be determined frequently. Adequate drainage must be assured in patients with urinary bladder outlet obstruction (such as prostatic hypertrophy).

Hemodialysis does not accelerate furosemide elimination.

DOSAGE AND ADMINISTRATION

Edema

Therapy should be individualized according to patient response to gain maximal therapeutic response and to determine the minimal dose needed to maintain that response.

Adults

The usual initial dose of furosemide is 20 mg to 80 mg given as a single dose. Ordinarily a prompt diuresis ensues. If needed, the same dose can be administered 6 to 8 hours later or the dose may be increased. The dose may be raised by 20 mg to 40 mg and given not sooner than 6 to 8 hours after the previous dose until the desired diuretic effect has been obtained. The individually determined single dose should then be given once or twice daily (e.g., at 8 am and 2 pm). The dose of furosemide may be carefully titrated up to 600 mg/day in patients with clinically severe edematous states.

Edema may be most efficiently and safely mobilized by giving furosemide on 2 to 4 consecutive days each week.

When doses exceeding 80 mg/day are given for prolonged periods, careful clinical observation and laboratory monitoring are particularly advisable. (See PRECAUTIONS: Laboratory Tests.)

Geriatric Patients

In general, dose selection for the elderly patient should be cautious, usually starting at the low end of the dosing range (see PRECAUTIONS: Geriatric Use).

Pediatric Patients

The usual initial dose of oral furosemide in pediatric patients is 2 mg/kg body weight, given as a single dose. If the diuretic response is not satisfactory after the initial dose, dosage may be increased by 1 or 2 mg/kg no sooner than 6 to 8 hours after the previous dose. Doses greater than 6 mg/kg body weight are not recommended. For maintenance therapy in pediatric patients, the dose should be adjusted to the minimum effective level.

Hypertension

Therapy should be individualized according to the patient's response to gain maximal therapeutic response and to determine the minimal dose needed to maintain the therapeutic response.

Adults

The usual initial dose of furosemide for hypertension is 80 mg, usually divided into 40 mg twice a day. Dosage should then be adjusted according to response. If response is not satisfactory, add other antihypertensive agents.

Changes in blood pressure must be carefully monitored when furosemide is used with other antihypertensive drugs, especially during initial therapy. To prevent excessive drop in blood pressure, the dosage of other agents should be reduced by at least 50 percent when furosemide is added to the regimen. As the blood pressure falls under the potentiating effect of furosemide, a further reduction in dosage or even discontinuation of other antihypertensive drugs may be necessary.

Geriatric Patients

In general, dose selection and dose adjustment for the elderly patient should be cautious, usually starting at the low end of the dosing range (see PRECAUTIONS: Geriatric Use).

HOW SUPPLIED

Furosemide Tablets, USP are available as tablets for oral administration. Each tablet for oral administration contains 20 mg, 40 mg or 80 mg of furosemide, USP.

The 20 mg tablets are white, round, unscored tablets debossed with M2. They are available as follows:

NDC 0378-0208-01
bottles of 100 tablets

NDC 0378-0208-10
bottles of 1000 tablets

The 40 mg tablets are white, round, scored tablets debossed with MYLAN over 216 on one side and the tablet and 40 on the other side. They are available as follows:

NDC 0378-0216-01
bottles of 100 tablets

NDC 0378-0216-10
bottles of 1000 tablets

The 80 mg tablets are white, round, scored tablets debossed with MYLAN over 232 on one side of the tablet and 80 on the other side. They are available as follows:

NDC 0378-0232-01
bottles of 100 tablets

NDC 0378-0232-05
bottles of 500 tablets

Store at 20° to 25°C (68° to 77°F). [See USP Controlled Room Temperature.]

Protect from light.

Dispense in a tight, light-resistant container as defined in the USP using a child-resistant closure. Exposure to light may cause a slight discoloration. Discolored tablets should not be dispensed.

Mylan Pharmaceuticals Inc.
Morgantown, WV 26505 U.S.A.

Revised: 6/2018
FUR:R29